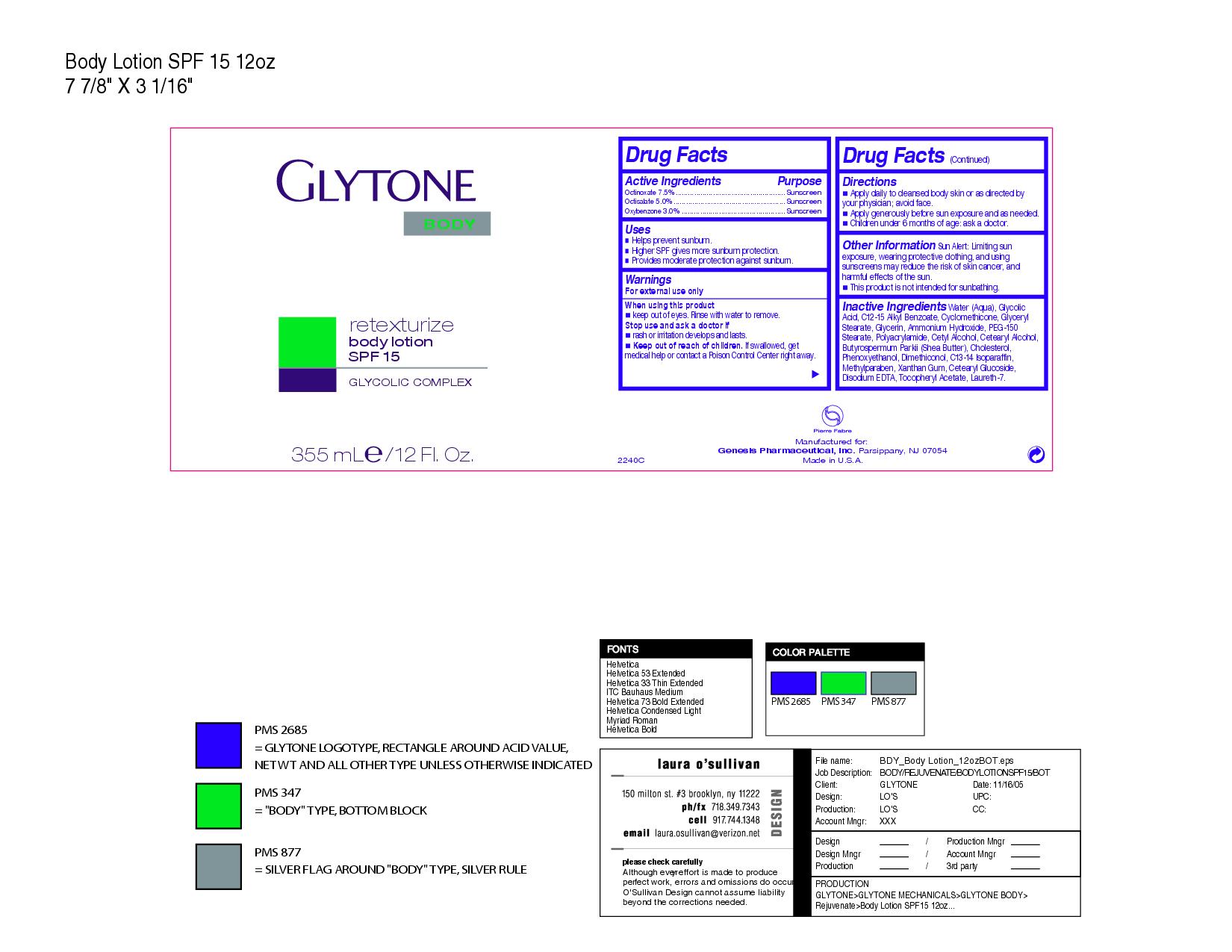 DRUG LABEL: glytone retexturize body
NDC: 64760-208 | Form: LOTION
Manufacturer: Glytone
Category: otc | Type: HUMAN OTC DRUG LABEL
Date: 20110201

ACTIVE INGREDIENTS: octinoxate 18.75 mL/250 mL; octisalate 12.5 mL/250 mL; oxybenzone 7.5 mL/250 mL
INACTIVE INGREDIENTS: WATER; GLYCOLIC ACID; ALKYL (C12-15) BENZOATE; CYCLOMETHICONE; GLYCERYL MONOSTEARATE; GLYCERIN; AMMONIA; POLYETHYLENE GLYCOL 6000; CETYL ALCOHOL; CETOSTEARYL ALCOHOL; SHEA BUTTER; CHOLESTEROL; PHENOXYETHANOL; C13-14 ISOPARAFFIN; METHYLPARABEN; XANTHAN GUM; CETEARYL GLUCOSIDE; EDETATE DISODIUM; .ALPHA.-TOCOPHEROL ACETATE, D-; LAURETH-7

Glytone Retexturize Body

Warnings

For external use only

When using this product

- keep out of eyes. Rinse with water to remove.

Stop use and ask a doctor if

- rash or irritation develops and lasts.
- Keep out of reach of children. If swallowed, get medical help or contact a Poison Control Center right away.

INACTIVE INGREDIENT

Inactive Ingredients Water (aqua), Glycolic Acid, C12-15 Alkyl Benzoate, Cyclomethicone, Glyceryl Stearate, Glycerin, Ammonium Hydroxide, PEG-150 Stearate, Polyacrylamide, Cetyl Alcohol, Cetearyl Alcohol, Butyrospermum Parkii (Shea Butter), Cholesterol, Phenozyethanol, Dimethiconol, C13-14 Isoparafin, Methylparaben, Xanthan gum, cetearyl glucoside, disodium EDTA, tocopheryl acetate, laureth-7

Uses

- Helps prevent sunburn.
- Higher SPF gives more sunburn protection
- Provides moderate protection against sunburn.

Active Ingredients Purpose

Octinoxate 7.5% Sunscreen

Octisalate 5.0% Sunscreen

Oxbenzone 3.0% Sunscreen

Directions

- Apply daily to cleansed body skin or as directed by your physician; avoid face
- Apply generously before sun exposure and as needed.
- Children under 6 months of age: ask a doctor.

Other Information

Sun alert: Limiting sun exposure, wearing protective clothing and using sunscreens may reduce the risk of skin cancer and harmful effects of the sun. This product is ot intended for sunbathing.

PACKAGE LABEL

Glytone retexturize body lotion

SPF 15

Glycolic complex

250 ml e/ 8.4 fl. oz.

Purpose sunscreen

Keep out of reach of children. If swallowed, get medical help or contact a Poison Control Center right away.